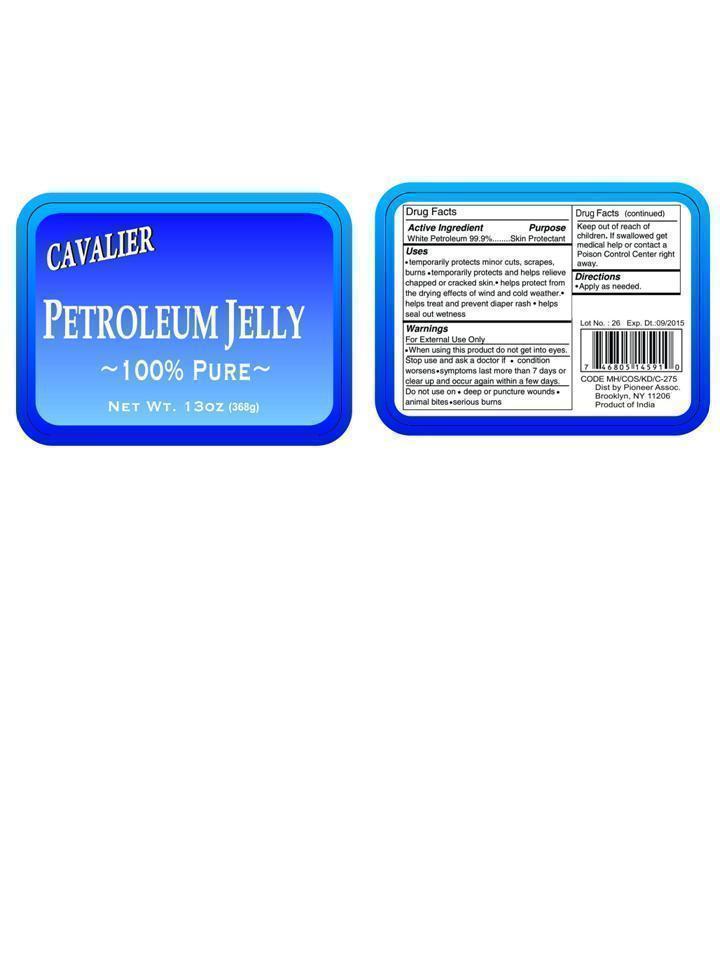 DRUG LABEL: CAVALIER
NDC: 53033-005 | Form: OINTMENT
Manufacturer: Imperial Bag & Paper Co.,LLC dba Pioneer Associates
Category: otc | Type: HUMAN OTC DRUG LABEL
Date: 20140314

ACTIVE INGREDIENTS: PETROLATUM 99.9 g/100 g

Drug Facts

Active Ingredient

White Petroleum 99.9%

Purpose

Skin protectant

Uses

- temporarily protects minor cuts, scrapes or burns.
- temporarily protects and helps relieve chapped or cracked skin and lips.
- helps protect from the drying effects of wind and cold weather.
- helps treat and prevent diaper rash
- helps seal out wetness

Warnings

For External Use Only.

- When using this product do not get into eyes.

Stop use and ask a doctor if

- condition worsens
- symptoms last more than 7 days or clear up and occur again within a few days

Do not use on

- deep or puncture wounds
- animal bites
- serious burns

Keep out of reach of children

If swallowed get medical help or contact a Poison Control Center right away.

Directions

- Apply as needed